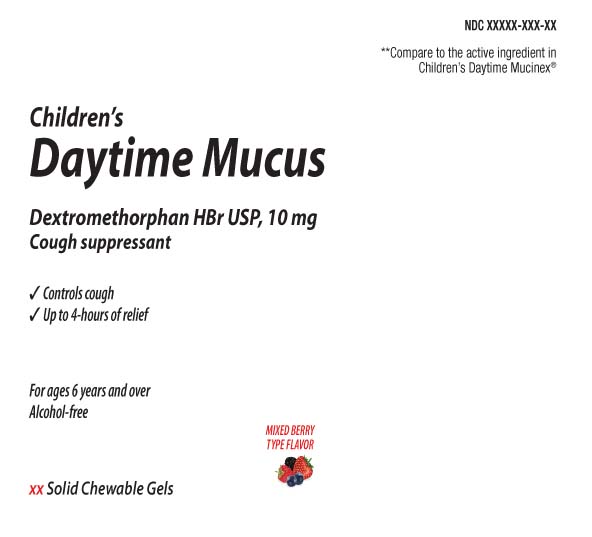 DRUG LABEL: Childrens Daytime Mucus
NDC: 0363-9358 | Form: CHEWABLE GEL
Manufacturer: Walgreens
Category: otc | Type: HUMAN OTC DRUG LABEL
Date: 20260212

ACTIVE INGREDIENTS: DEXTROMETHORPHAN HYDROBROMIDE 10 mg/1 1
INACTIVE INGREDIENTS: ANHYDROUS CITRIC ACID; WATER; SUCRALOSE; FD&C BLUE NO. 1; MALIC ACID; CORN SYRUP; ALCOHOL; FD&C RED NO. 40; SUCROSE; AMMONIUM GLYCYRRHIZATE; GLYCERIN; GLYCYRRHIZIN; MALTODEXTRIN; MEDIUM-CHAIN TRIGLYCERIDES; PECTIN; PROPYLENE GLYCOL; SORBITOL SOLUTION; TRISODIUM CITRATE DIHYDRATE

Drug Facts

Active ingredients (in each chewable gel)

Dextromethorphan HBr 10 mg

Purpose

Cough suppressant

Uses

- temporarily relieves cough due to minor throat and bronchial irritation

Warnings

Do not use

if you are now taking a prescription monoamine oxidase inhibitor (MAOI) (certain drugs for depression, psychiatric or emotional conditions, or Parkinson’s disease),or for 2 weeks after stopping the MAOI drug. If you do not know if your prescription drug contains an MAOI, ask a doctor or pharmacist before giving this product.

Ask a doctor before use if you have

- cough that occurs with too much phlegm (mucus)
- persistent or chronic cough such as occurs with smoking, asthma, chronic bronchitis or emphysema

When using this product

do not use more than directed.

Stop use and ask a doctor if

cough lasts more than 7 days, comes back, or occurs with fever, rash or headache that lasts.These could be signs of a serious condition.

If pregnant or breast-feeding,

ask a health professional before use.

Keep out of reach of children.

In case of overdose, get medical help or contact a Poison Control Center (1-800-222-1222) right away.

Directions

- take every 4 hours or as directed by a doctor
- chew thoroughly before swallowing
- adults and children 12 years of age and over: 2 chewable gels every 4 hours, not to exceed 12 chewable gels in any 24-hour period
- children 6 years of age and over: 1 chewable gel every 4 hours, not to exceed 6 chewable gels in any 24-hour period
- children under 6 years of age: do not use

Other information

- each chewable gel contains: sodium 8 mg
- store between 20-25ºC (68-77ºF). Do not refrigerate

Inactive ingredients

alcohol, ammonium glycyrrhizate, anhydrous citric acid, corn syrup, FD&C Blue No. 1, FD&C Red No. 40, flavors, glycerin, glycyrrhizin, malic acid, maltodextrin, medium-chain triglycerides, pectin, propylene glycol, purified water, sorbitol solution, sucralose, sucrose, trisodium citrate dihydrate

Questions or comments?

Call 1-877-753-3929 Monday-Friday 9AM-5PM EST

Principal Display Panel

**Compare to the active ingredient in Children's Daytime Mucinex®

Children's

Daytime Mucus

Dextromethorphan HBr 10 mg

Cough Suppressant

- Controls cough
- Up to 4-hours of relief

For ages 6 years and over

Alcohol-free

Solid Chewable Gels

Mixed Berry Flavor

FL OZ (mL)

**This product is not manufactured or distributed by RB Health (US) LLC,distributor of Children's Daytime Mucinex®.

TAMPER EVIDENT: DO NOT USE IF PRINTED SAFETY SEAL IS BROKEN OR MISSING.

DISTRIBUTED BY: WALGREEN CO

Package Label

WALGREENS Daytime Mucus Mixed Berry Flavor